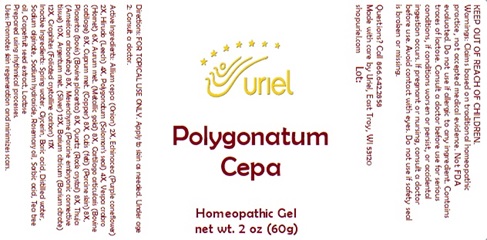 DRUG LABEL: Polygonatum Cepa
NDC: 48951-8310 | Form: GEL
Manufacturer: Uriel Pharmacy Inc.
Category: homeopathic | Type: HUMAN OTC DRUG LABEL
Date: 20251117

ACTIVE INGREDIENTS: ONION 2 [hp_X]/1 g; ECHINACEA ANGUSTIFOLIA 2 [hp_X]/1 g; HIRUDIN 4 [hp_X]/1 g; POLYGONATUM CYRTONEMA ROOT 4 [hp_X]/1 g; VESPA CRABRO 6 [hp_X]/1 g; GOLD 8 [hp_X]/1 g; BOS TAURUS CARTILAGE 8 [hp_X]/1 g; COPPER 8 [hp_X]/1 g; SUS SCROFA SKIN 8 [hp_X]/1 g; BOS TAURUS PLACENTA 8 [hp_X]/1 g; SILICON DIOXIDE 8 [hp_X]/1 g; THUJA OCCIDENTALIS WHOLE 8 [hp_X]/1 g; SILVER 12 [hp_X]/1 g; BARIUM CITRATE 12 [hp_X]/1 g; GRAPHITE 17 [hp_X]/1 g
INACTIVE INGREDIENTS: SODIUM HYDROXIDE; WATER; GLYCERIN; SODIUM ALGINATE; ROSEMARY OIL; BORIC ACID; CITRUS PARADISI SEED; TEA TREE OIL; SORBIC ACID

Polygonatum Cepa

INDICATIONS AND USAGE

Directions: FOR TOPICAL USE ONLY

DOSAGE AND ADMINISTRATION

Apply to skin as needed. Under age 2: Consult a doctor.

ACTIVE INGREDIENT

Active Ingredients: Allium cepa (Onion) 2X, Echinacea (Purple coneflower) 2X, Hirudo (Leech) 4X, Polygonatum (Solomon’s seal) 4X, Vespa crabro (Hornet) 6X, Aurum met. (Metallic gold) 8X, Cartilago articularis (Bovine cartilage) 8X, Cuprum met. (Copper) 8X, Cutis (feti) (Porcine skin) 8X, Placenta (bovis) (Bovine placenta) 8X, Quartz (Rock crystal) 8X, Thuja (American arborvitae) 8X, Mesenchyme (Porcine embryonic connective tissue) 10X, Argentum met. (Silver) 12X, Barium citricum (Barium citrate) 12X, Graphites (Foliated crystalline carbon) 17X

INACTIVE INGREDIENT

Inactive Ingredients: Distilled water, Glycerin, Boric acid, Sodium hydroxide, Sodium alginate, Rosemary oil, Sorbic acid, Tea tree oil, Grapefruit seed extract, Lactose

"prepared using rhythmical processes"

PURPOSE

Uses: Promotes skin regeneration and minimizes scars.

WARNINGS

Warnings: Claims based on traditional homeopathic practice, not accepted medical evidence. Not FDA evaluated. Do not use if allergic to any ingredient. Contains traces of lactose. Consult a doctor before use for serious conditions, if conditions worsen or persist, or accidental ingestion occurs. If pregnant or nursing, consult a doctor before use. Avoid contact with eyes. Do not use if safety seal is broken or missing.

KEEP OUT OF REACH OF CHILDREN.

QUESTIONS

Questions? Call 866.642.2858 Made with care by Uriel, East Troy, WI 53120 shopuriel.com Lot: